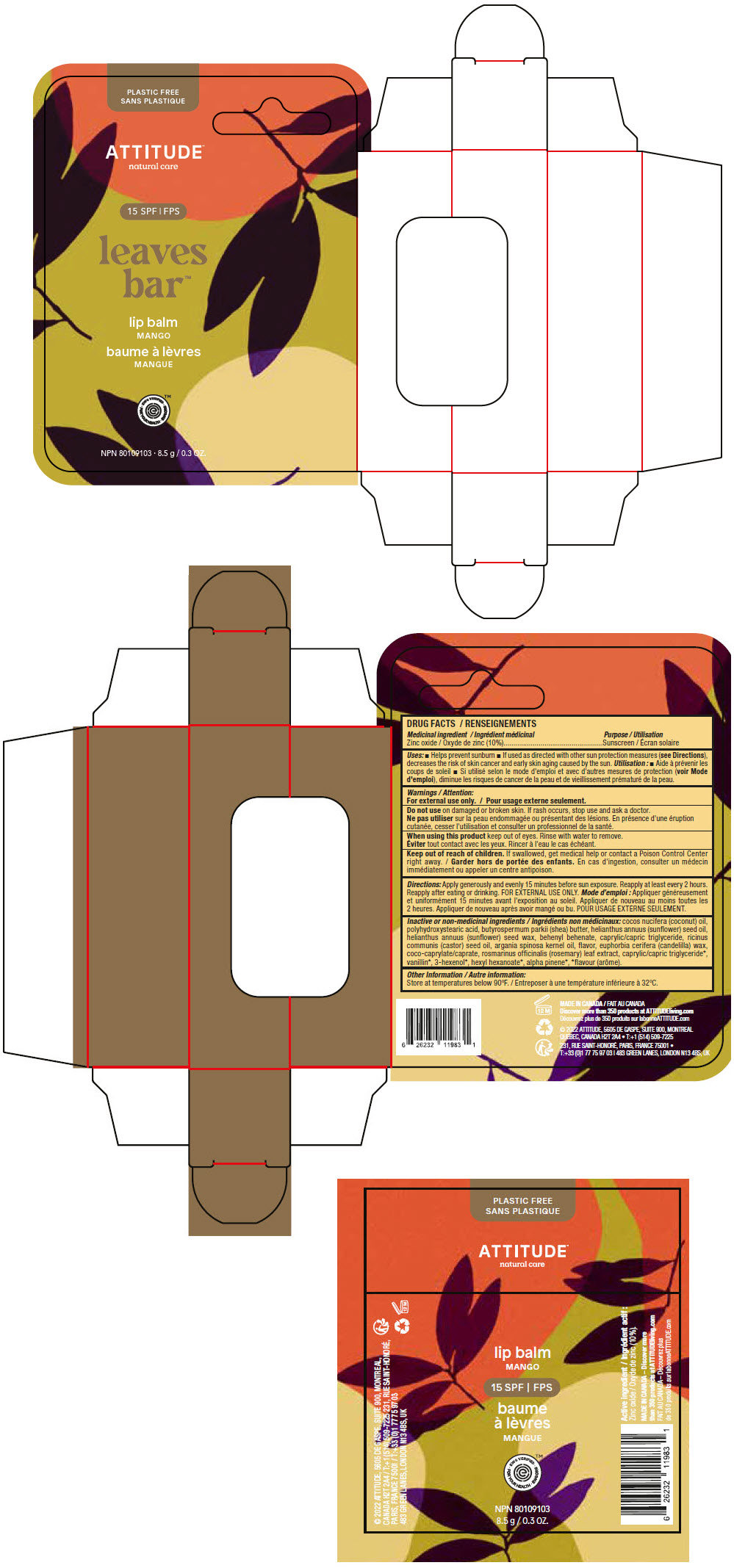 DRUG LABEL: Attitude - Leaves Bar - Lip Balm - SPF 15 - Mango
NDC: 61649-983 | Form: STICK
Manufacturer: 9055-7588 Québec Inc. DBA Attitude
Category: otc | Type: HUMAN OTC DRUG LABEL
Date: 20251203

ACTIVE INGREDIENTS: ZINC OXIDE 10 g/100 g
INACTIVE INGREDIENTS: COCONUT OIL; POLYHYDROXYSTEARIC ACID (2300 MW); SHEA BUTTER; SUNFLOWER OIL; HELIANTHUS ANNUUS SEED WAX; BEHENYL BEHENATE; MEDIUM-CHAIN TRIGLYCERIDES; CASTOR OIL; ARGAN OIL; CANDELILLA WAX; COCOYL CAPRYLOCAPRATE; ROSEMARY; VANILLIN; 3-HEXEN-1-OL, (3Z)-; HEXYL HEXANOATE; .ALPHA.-PINENE

ATTITUDE Leaves Bar Lip Balm - Mango - SPF 15

DRUG FACTS

Medicinal ingredient

Zinc oxide (10%)

Purpose

Sunscreen

Uses

- Helps prevent sunburn
- If used as directed with other sun protection measures (see Directions), decreases the risk of skin cancer and early skin aging caused by the sun.

Warnings

For external use only.

DO NOT USE

Do not useon damaged or broken skin. If rash occurs, stop use and ask a doctor.

WHEN USING

When using this productkeep out of eyes. Rinse with water to remove.

Keep out of reach of children.If swallowed, get medical help or contact a Poison Control Center right away.

Directions

Apply generously and evenly 15 minutes before sun exposure. Reapply at least every 2 hours. Reapply after eating or drinking. FOR EXTERNAL USE ONLY.

Inactive or non-medicinal ingredients

cocos nucifera (coconut) oil, polyhydroxystearic acid, butyrospermum parkii (shea) butter, helianthus annuus (sunflower) seed oil, helianthus annuus (sunflower) seed wax, behenyl behenate, caprylic/capric triglyceride, ricinus communis (castor) seed oil, argania spinosa kernel oil, flavor, euphorbia cerifera (candelilla) wax, coco-caprylate/caprate, rosmarinus officinalis (rosemary) leaf extract, caprylic/capric triglyceride [*flavour] , vanillin , 3-hexenol , hexyl hexanoate , alpha pinene .

Other Information

Store at temperatures below 90°F.

PRINCIPAL DISPLAY PANEL - 8.5 g Tube Carton

PLASTIC FREE

ATTITUDE™
natural care

15 SPF

leaves
bar™

lip balm
MANGO

• EWG VERIFIED •
FOR YOUR HEALTH • EWG.ORG

NPN 80109103 8.5 g / 0.3 OZ.